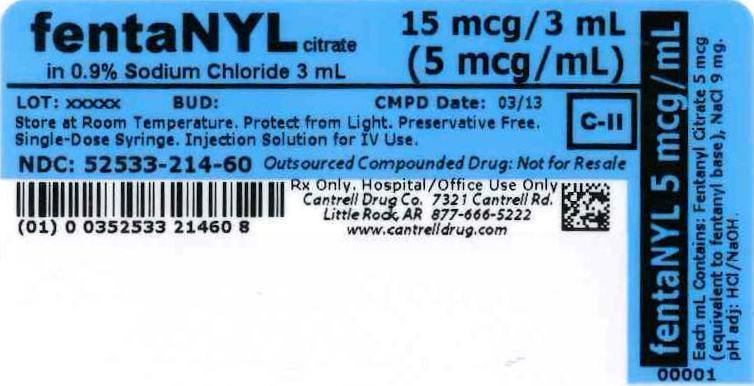 DRUG LABEL: FENTANYL CITRATE
NDC: 52533-214 | Form: INJECTION, SOLUTION
Manufacturer: Cantrell Drug Company
Category: prescription | Type: HUMAN PRESCRIPTION DRUG LABEL
Date: 20140813
DEA Schedule: CII

ACTIVE INGREDIENTS: FENTANYL CITRATE 5 ug/1 mL
INACTIVE INGREDIENTS: Sodium Chloride 9 mg/1 mL; Water

Fentanyl Citrate 5 mcg/mL in 0.9% Sodium Chloride 3 mL Syringe